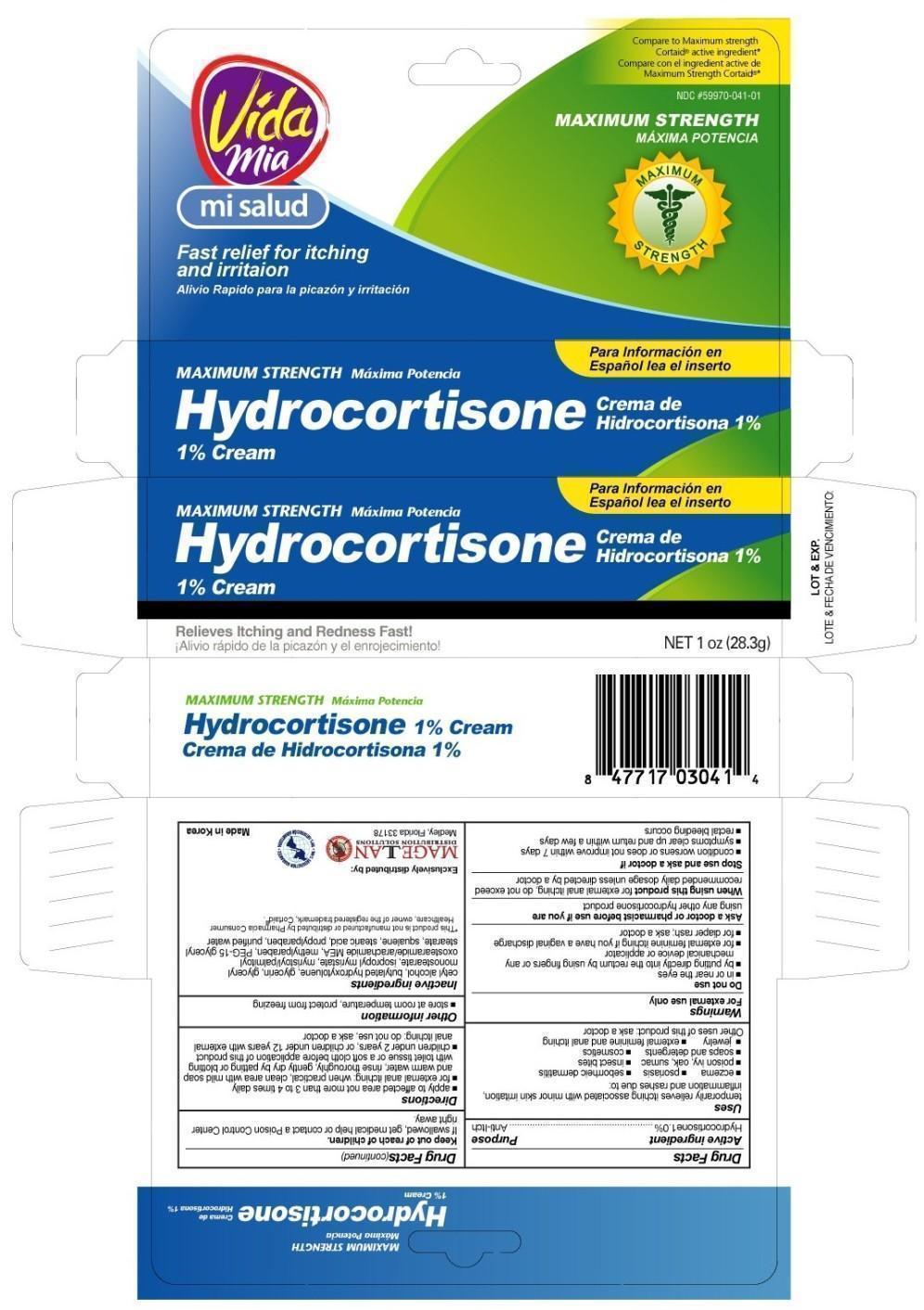 DRUG LABEL: Hydrocortisone
NDC: 59970-041 | Form: CREAM
Manufacturer: Navarro Discount Pharmacies,LLC
Category: otc | Type: HUMAN OTC DRUG LABEL
Date: 20120816

ACTIVE INGREDIENTS: Hydrocortisone 1 g/100 g
INACTIVE INGREDIENTS: Cetyl alcohol; BUTYLATED HYDROXYTOLUENE; GLYCERIN; GLYCERYL MONOSTEARATE; ISOPROPYL MYRISTATE; METHYLPARABEN; SQUALANE; STEARIC ACID; PROPYLPARABEN; WATER

Drug Facts

Active Ingredient

Hydrocortisone 1%

Purpose

Anti-itch

Uses

temporarily relieves itching associated with minor sin irritation, inflammation and rashes due to:

- eczema
- psoriasis
- seborrheic dermatitis
- poison ivy, oak, sumac
- insect bites
- soaps and detergents
- cosmetics
- jewelry
- external feminine and anal itching

Other uses of this product: ask a doctor

Warnings

For external use only

Do not use

- in or near the eyes
- by putting directly into the rectum by using fingers or any mechanical device or applicator
- for external feminine itching if you have a vaginal discharge
- for diaper rash; ask a doctor

Ask a doctor or pharmacist before use if you are

using any other hydrocortisone product

When using this product

for external anal itching, do not exceed recommended daily dosage unless directed by a doctor

Stop use and ask a doctor if

- condition worsens or does not improve within 7 days
- symptoms clear up and return within a few days
- rectal bleeding occurs

Keep out of reach of children

If swallowed, get medical help or contact a Poison Control right away.

Directions

- apply to affected area not more than 3 to 4 times daily
- for external anal itching: when practical, clean area with mild soap and warm water, rinse thoroughly, gently dry by patting or blotting with toilet tissue or a soft cloth before application of this product
- children under 2 years, or children under 12 years with external anal itching: do not use, ask a doctor

Other information

- store at room temperature, protect from freezing

INACTIVE INGREDIENT

Cetyl alcohol, Butylated hydroxytoluene, Glycerin, Glyceryl monostearate, Isopropyl myristate, Myristoyl/palmitoyl/oxostearamide/arachamide MEA, Methylparaben, PEG-15 glyceryl stearate, Squalane, Stearic acid, Propylparaben, Purified water

PACKAGE LABEL

Hydrocortisone